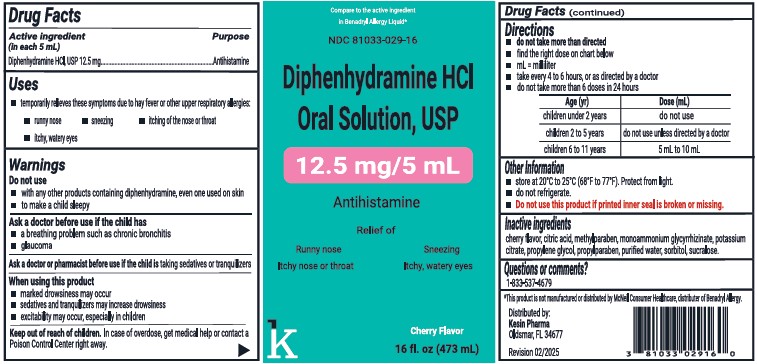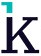 DRUG LABEL: Diphenhydramine HCl Oral Solution
NDC: 81033-029 | Form: SOLUTION
Manufacturer: Kesin Pharma Corporation
Category: otc | Type: HUMAN OTC DRUG LABEL
Date: 20250304

ACTIVE INGREDIENTS: DIPHENHYDRAMINE HCL 12.5 mg/5 mL
INACTIVE INGREDIENTS: METHYLPARABEN; SUCRALOSE; PROPYLENE GLYCOL; PROPYLPARABEN; ANHYDROUS CITRIC ACID; SORBITOL; AMMONIUM GLYCYRRHIZATE; POTASSIUM CITRATE

Diphenhydramine HCl Oral Solution, USP

Drug Facts

Active Ingredients (in each 5 mL)

Diphenhydramine HCl, USP 12.5 mg

Purpose

Antihistamine

Uses

- temporarily relieves these symptoms due to hay fever or other upper respiratory allergies:
- runny nose
- sneezing
- itching of the nose or throat
- itchy, watery eyes

Warnings

Do not use

- with any other products containing diphenhydramine, even one used on skin
- to make a child sleepy

Ask a doctor before use if the child has

- a breathing problem such as chronic bronchitis
- glaucoma

Ask a doctor or pharmacist before use if the child is taking sedastives or tranquilizers

When using this product

- marked drowsiness may occur
- sedatives and tranquilizers may increase drowsiness
- excitability may occur, especially in children

Keep out of reach of children.

Overdose

In case of overdose, get medical help or contact a Poison Control Center right away.

DIRECTIONS

- do not take more than directed
- find the right dose on the chart below
- mL = milliliter
- take every 4 to 6 hurs, or as directed by a doctor
- do not take more than 6 doses in 24 hours

Age (yr) | Doses (mL)
children under 2 years | do not use
children 2 to 5 years | do not use unless directed by a doctor
children 6 to 11 years | 5 mL to 10 mL

Other Information

- store at 20ºC to 25ºC (68ºF to 77ºF). Protect from light.
- do not refrigerate
- Do not use this product if printed inner seal is broken or missing.

Inactive ingredients

cherry flavor, citric acid, methylparaben, monoammonium glcyrrhizinate, potassium citrate, propylene glycol, polyparaben, purified water, sorbitol, sucralose.

Questions or comments?

1-833-537-4679

*This product is not manufactured by McNeil Consumer Healthcare, distributer of Benadryl Allergy.

Distributed by:

Kesin Pharma

Oldsmar, FL 34677

Revision 02/2025

PACKAGE LABEL

NDC 81033-029-16

Diphenhydramine HCl

Oral Solution, USP

12.5 mg/5 mL

Antihistamine

Cherry Flavor

16 fl oz. (473 mL)